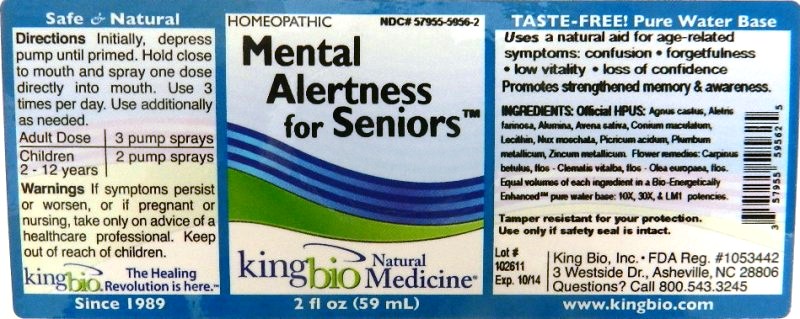 DRUG LABEL: Mental Alertness for Seniors
NDC: 57955-5956 | Form: LIQUID
Manufacturer: King Bio Inc.
Category: homeopathic | Type: HUMAN OTC DRUG LABEL
Date: 20111205

ACTIVE INGREDIENTS: CHASTE TREE 10 [hp_X]/59 mL; ALETRIS FARINOSA ROOT 10 [hp_X]/59 mL; ALUMINUM OXIDE 10 [hp_X]/59 mL; AVENA SATIVA FLOWERING TOP 10 [hp_X]/59 mL; CONIUM MACULATUM FLOWERING TOP 10 [hp_X]/59 mL; EGG PHOSPHOLIPIDS 10 [hp_X]/59 mL; NUTMEG 10 [hp_X]/59 mL; TRINITROPHENOL 10 [hp_X]/59 mL; LEAD 10 [hp_X]/59 mL; ZINC 10 [hp_X]/59 mL; CARPINUS BETULUS FLOWERING TOP 10 [hp_X]/59 mL; CLEMATIS VITALBA FLOWER 10 [hp_X]/59 mL; OLEA EUROPAEA FLOWER 10 [hp_X]/59 mL
INACTIVE INGREDIENTS: WATER

Mental Alertness for Seniors

Active Ingredients

Official HPUS: Agnus castus, Aletris farinosa, Alumina, Avena sativa, Conium maculatum, Lecithin, Nux moschata, Picricum acidum, Plumbum metallicum and Zincum metallicum.

Flower remedies: Carpinus betulus, flos, Clematis vitalba, flos and Olea europaea, flos.

Reference image alertness.jpg

Inactive Ingredient

Equal volumes of each ingredient in a Bio-Energetically Enhanced pure water base:10X, 30X, and LM1 potencies.

Reference image alertness.jpg

Dosage and Administration

Directions initially, depress pump until primed. Hold close to mouth and spray one dose directly into mouth. Use 3 times per day. Use additionally as needed.

Adult Dose 3 pump sprays

children (2-12years) 2 pump sprays

Reference image alertness.jpg

Purpose

Uses a natural aid for age-related symptoms: confusion, forgetfulness, low vitality, loss of confidence.

Promotes strengthened memory and awareness.

Reference image alertness.jpg

Warnings

If symptoms persist or worsen, or if pregnant or nursing, take only on advice of a healthcare professional.

Tamper resistant for your protection. Use only if safety seal is intact.

Reference image alertness.jpg

Keep out of reach of children.

Reference image alertness.jpg

Indications and Usage

Uses a natural aid for age-related symptoms:

- Confusion
- forgetfulness
- low vitality
- loss of confidence

Promotes strengthened memory and awareness.
Reference image alertness.jpg

PACKAGE LABEL

King Bio, Inc.

3 Westside Drive,

Asheville, NC 28806

Questions? Call 800.543.3245

www.kingbio.com